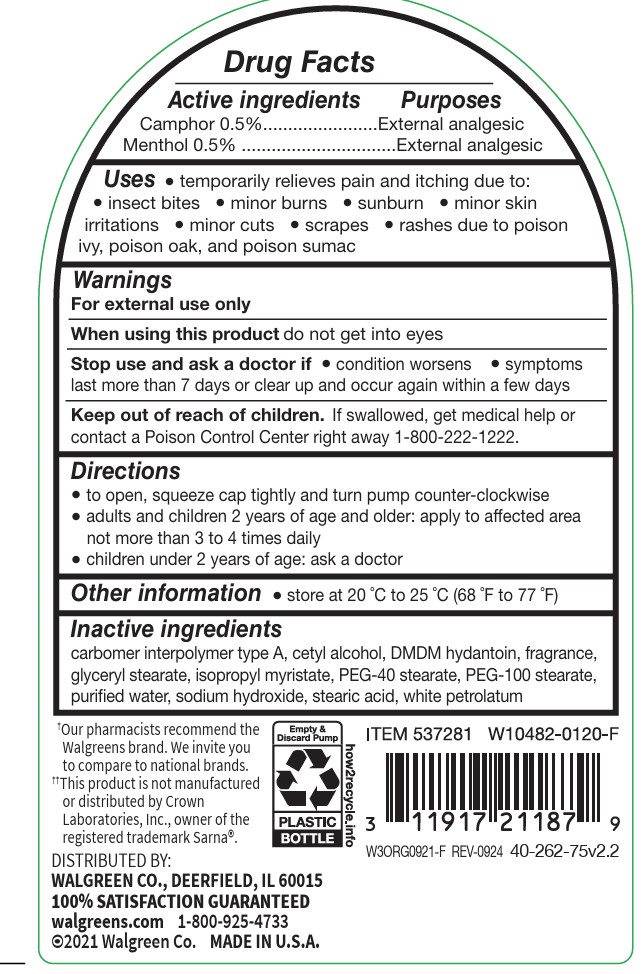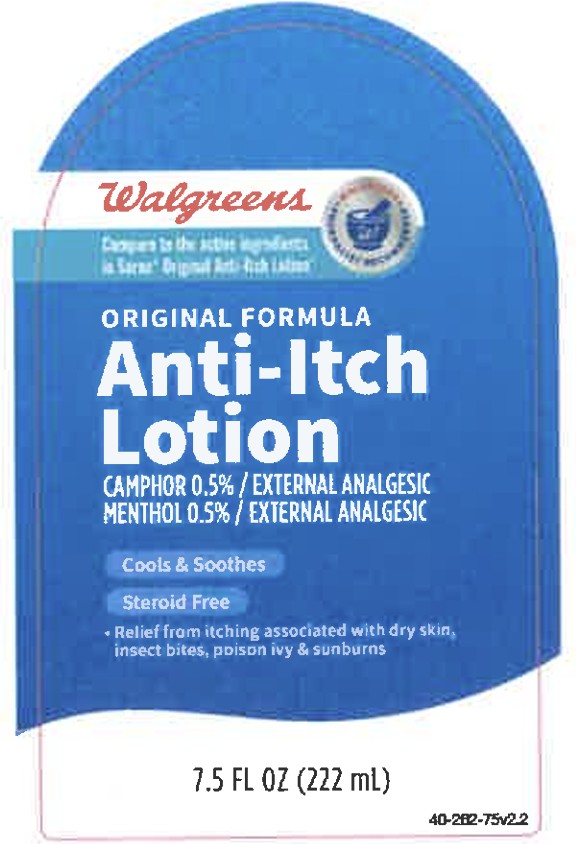 DRUG LABEL: Walgreen Anti Itch
NDC: 0363-4262 | Form: LOTION
Manufacturer: Walgreens
Category: otc | Type: HUMAN OTC DRUG LABEL
Date: 20251119

ACTIVE INGREDIENTS: CAMPHOR (SYNTHETIC) 0.5 g/100 g; MENTHOL 0.5 g/100 g
INACTIVE INGREDIENTS: SODIUM HYDROXIDE; DMDM HYDANTOIN; GLYCERYL STEARATE SE; PEG-100 STEARATE; PEG-40 STEARATE; CARBOMER COPOLYMER TYPE A; WATER; CETYL ALCOHOL; PETROLATUM; ISOPROPYL MYRISTATE; STEARIC ACID

Walgreen Anti-Itch Lotion

ACTIVE INGREDIENT

Camphor 0.5%

Menthol 0.5%

INDICATIONS AND USAGE

temporary relieves pain and itching due to:

insect bites

minor burns

sunburn

minor skin irritations

minor cuts

scrapes

rashes due to poison ivy, poison oak, and poison sumac

WARNINGS

For external use only

ASK DOCTOR

on chicken pox

on measles

WHEN USING

do not get into eyes

STOP USE

condition worsens

symptoms last more than 7 days or clear up and occur again within a few days

KEEP OUT OF REACH OF CHILDREN

If swallowed, get medical help or contact a Poison Control Center right away.

PURPOSE

Anti-itch

External Analgesic

Directions

to open, squeeze cap tightly and turn pump counter-clockwise

adults and children 2 years and older: apply to affected area not more than 3 to 4 times daily

children under 2 years: ask a doctor

Other information

store at 20 °C to 25 °C (68 °F to 77 °F)

INACTIVE INGREDIENT

carbomber interpolymer type A, cetyl alcohol, DMDM hydantoin, fragrance, glyceryl stearate, isopropyl myristate, PEG-40 stearate, PEG-100 stearate,purified water, sodium hydroxide, stearic acid, white petrolatum

PACKAGE LABEL

Cools and soothes , steriod free

relief from itching associated with dry skin, insect bites, poison ivy, and sunburns